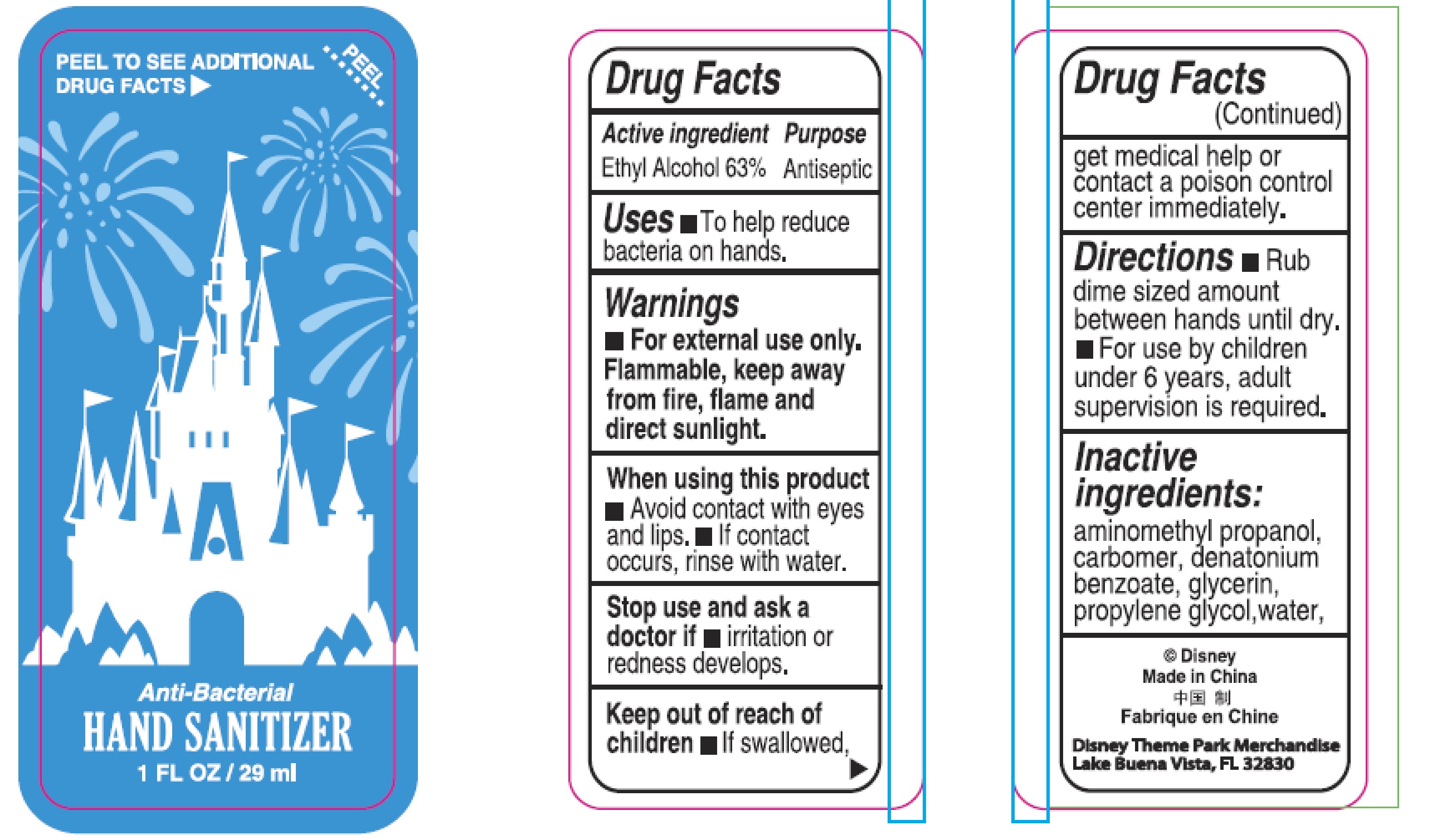 DRUG LABEL: Anti-Bacterial HAND SANITIZER
NDC: 72707-029 | Form: GEL
Manufacturer: DISNEY DESTINATIONS,LLC
Category: otc | Type: HUMAN OTC DRUG LABEL
Date: 20250407

ACTIVE INGREDIENTS: ALCOHOL 63 mL/100 mL
INACTIVE INGREDIENTS: CARBOMER COPOLYMER TYPE A (ALLYL PENTAERYTHRITOL CROSSLINKED); AMINOMETHYLPROPANOL; DENATONIUM BENZOATE; WATER; GLYCERIN; PROPYLENE GLYCOL

72707-029, Anti-Bacterial
HAND SANITIZER

Active ingredient

Ethyl Alcohol 63%

Purpose

Antiseptic

Uses

To help reduce bacteria on hands.

Warnings

- For external use only.
- Flammable, keep away from fire, flame and direct sunlight.

When using this product

- Avoid contact with eyes and lips.
- If contact occurs, rinse with water.

Stop use and ask a doctor if if irritation or redness develops.

Keep out of reach of children If swallowed, get medical help or contact a poison control center immediately.

Directions

- Place enough to cover both hands in the palm, and rub hands together until dry.
- Children under 6 years of age should be supervised by adults when applying this product.

Inactive ingredients:

aminomethyl propanol, carbomer, denatonium benzoate, glycerin, propylene glycol, water.